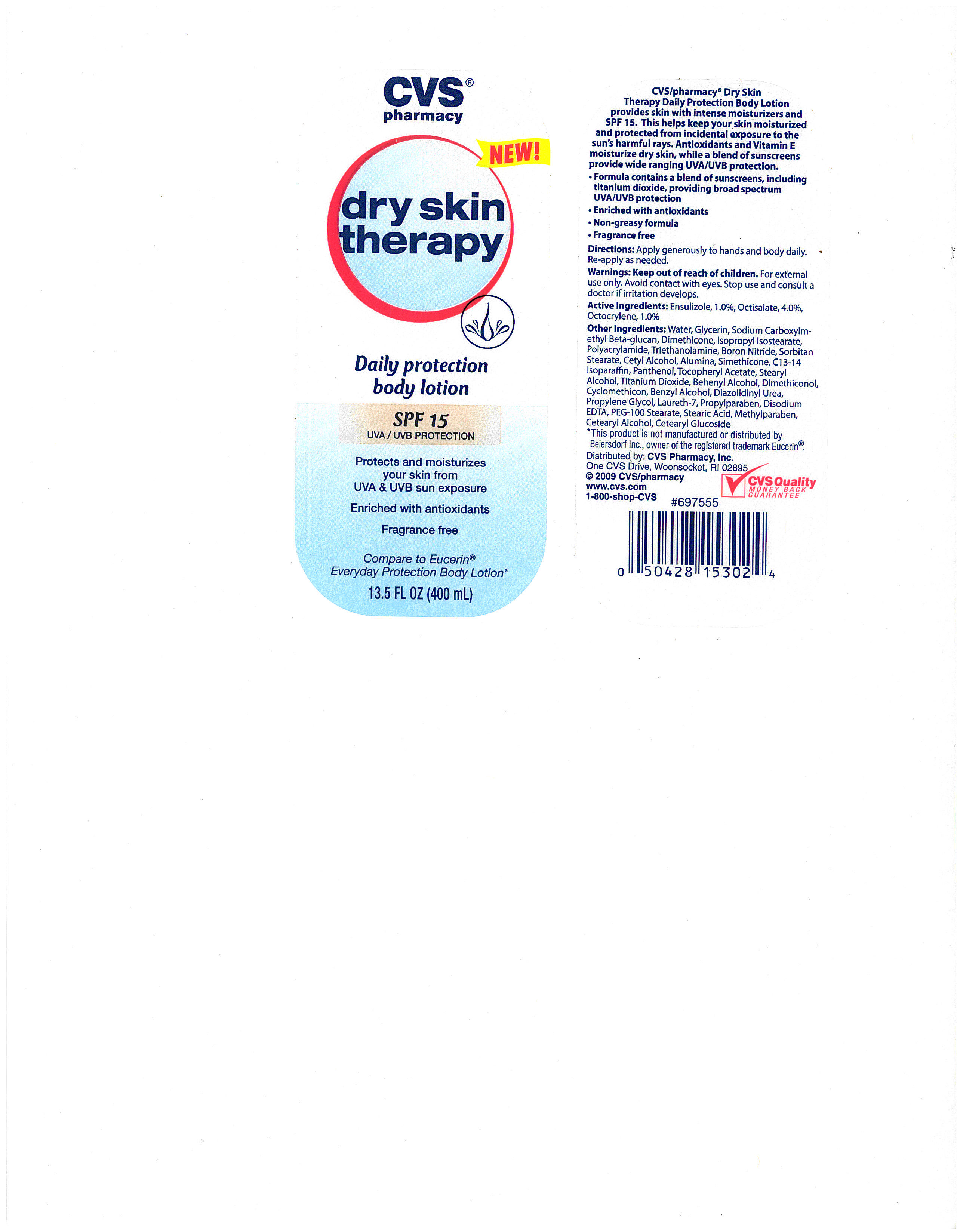 DRUG LABEL: CVS DRY SKIN THERAPY WITH SPF 15
NDC: 59779-317 | Form: LOTION
Manufacturer: CVS Pharmacy
Category: otc | Type: HUMAN OTC DRUG LABEL
Date: 20110719

ACTIVE INGREDIENTS: ENSULIZOLE 10 mg/1 mL; OCTISALATE 40 mg/1 mL; OCTOCRYLENE 10 mg/1 mL
INACTIVE INGREDIENTS: WATER; GLYCERIN; EDETATE DISODIUM; TEA LEAF; TITANIUM DIOXIDE; GLYCERYL ISOSTEARATE; ALUMINUM OXIDE; DIMETHICONE; STEARYL ALCOHOL; SORBITAN MONOSTEARATE; CETYL ALCOHOL; ALPHA-TOCOPHEROL ACETATE; STEAROXYTRIMETHYLSILANE; POLYOXYL 100 STEARATE; STEARIC ACID; BENZYL ALCOHOL; PANTHENOL; PROPYLENE GLYCOL; PROPYLPARABEN; METHYLPARABEN; DIAZOLIDINYL UREA; .ALPHA.-GLUCAN OLIGOSACCHARIDE

drug facts

ACTIVE INGREDIENT

Active Ingredients: Ensulizole, 1.0%, Octisaltae, 4.0%, Octocrylene, 1.0%

PURPOSE

CVS/pharmacy Dry Skin Therapy Daily Protection Body Lotion provides skin
with intense moisturizers and SPF 15. This helps keep your skin moisturized
and protected from incidental exposure to the sun's harmful rays. Antioxidants
and Vitamine E moisturize dry skin, while a blend of sunscreens provide wide
ranging UVA/UVB protection.
-Formula contains a blend of sunscreens, including titanium dioxide, providing
broad spectrum UVA/UVB protection
- Enriched with antioxidants
- Non-greasy formula
- Fragrance free

Warnings: Keep out of reach of children.

INDICATIONS AND USAGE

CVS/pharmacy Dry Skin Therapy Daily Protection Body Lotion provides skin
with intense moisturizers and SPF 15. This helps keep your skin moisturized
and protected from incidental exposure to the sun's harmful rays. Antioxidants
and Vitamine E moisturize dry skin, while a blend of sunscreens provide wide
ranging UVA/UVB protection.
-Formula contains a blend of sunscreens, including titanium dioxide, providing
broad spectrum UVA/UVB protection
- Enriched with antioxidants
- Non-greasy formula
- Fragrance free

Warnings
Keep out of reach of children.
For external use only.
Avoid contact with eyes.
Stop use and consult a doctor if irritation develops.

Directions
Apply generously to hands and body daily.
Reapply as needed.

INACTIVE INGREDIENT

Other Ingredients
Water, Glycerin, Sodium Carboxylmethyl Beta-Glucan, Dimethicone, Isopropyl Isostearate,
Polyacrylamide, Triethanolamine, Boron Nitride, Sorbitan Stearate, Cetyl Alcohol, Alumina,
Simethicone, C13-14 Isoparaffin, Panthenol, Tocopheryl Acetate, Stearyl Alcohol, Titanium Dioxide,
Behenyl Alcohol, Dimethiconol, Cyclomethicon, Benzyl Alcohol, Diazolidinyl Urea, Propylene Glycol,
Laureth-7, Propylparaben, Disodium EDTA, PEG-100 Stearate, Stearic Acid, Methylparaben, Cetaryl Alcohol,
Cetaryl Glucoside